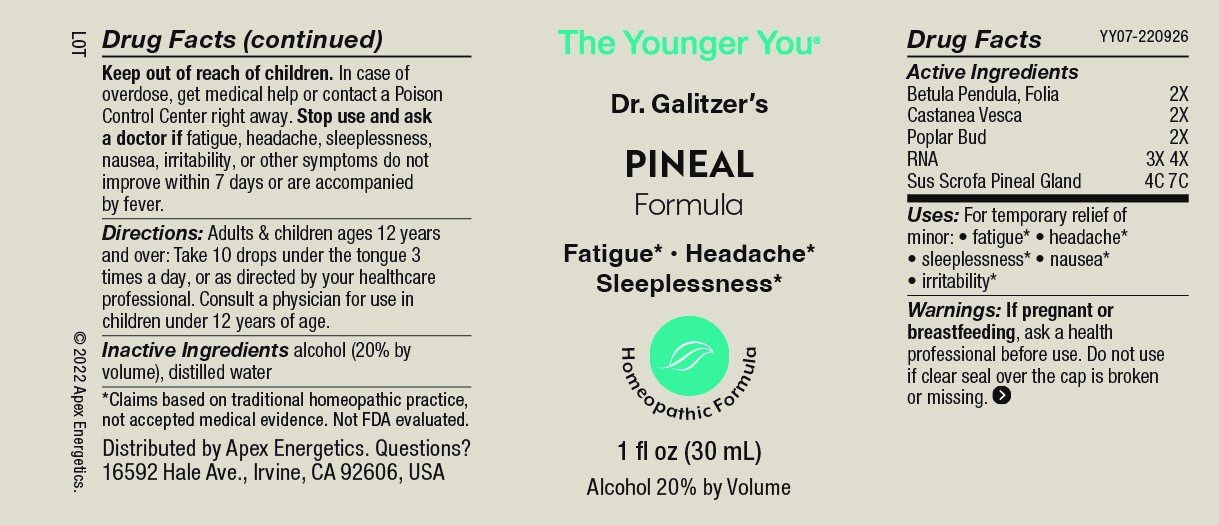 DRUG LABEL: PINEAL Formula
NDC: 63479-2507 | Form: SOLUTION/ DROPS
Manufacturer: Apex Energetics Inc.
Category: homeopathic | Type: HUMAN OTC DRUG LABEL
Date: 20240108

ACTIVE INGREDIENTS: POPULUS BALSAMIFERA LEAF BUD 2 [hp_X]/1 mL; SACCHAROMYCES CEREVISIAE RNA 4 [hp_X]/1 mL; BETULA PENDULA LEAF 2 [hp_X]/1 mL; SUS SCROFA PINEAL GLAND 7 [hp_C]/1 mL; CASTANEA SATIVA LEAF 2 [hp_X]/1 mL
INACTIVE INGREDIENTS: WATER; ALCOHOL

YY07

Active Ingredients
Betula Pendula, Folia | 2X
Castanea Vesca | 2X
Poplar Bud | 2X
RNA | 3X 4X
Sus Scrofa Pineal Gland | 4C 7C

INDICATIONS AND USAGE

Uses:

For temporary relief of minor:

fatigue*

headache*
sleeplessness*

nausea*
irritability*

*Claims based on traditional homeopathic practice, not accepted medical evidence. Not FDA evaluated.

Warnings:

PREGNANCY OR BREAST FEEDING

If pregnant or breastfeeding, ask a health professional before use.

Do not use if clear seal over the cap is broken or missing.

Keep out of reach of children. In case of overdose, get medical help or contact a Poison Control Center right away.

Stop use and ask a doctor if fatigue, headache,sleeplessness, nausea, irritability, or other symptoms do not improve within 7 days or are accompanied by fever.

Directions:

Adults & children ages 12 years and over: Take 10 drops under the tongue 3 times a day, or as directed by your healthcare professional. Consult a physician for use in children under 12 years of age.

Inactive Ingredients

alcohol (20% by volume), distilled water

Distributed by Apex Energetics. Questions?
16592 Hale Ave., Irvine, CA 92606, USA

PACKAGE LABEL

The Younger You®

Dr. Galitzer’s

PINEAL

Formula

Fatigue*

Headache*

Sleeplessness*

Homeopathic Formula

1 fl oz (30 mL)

Alcohol 20% by Volume